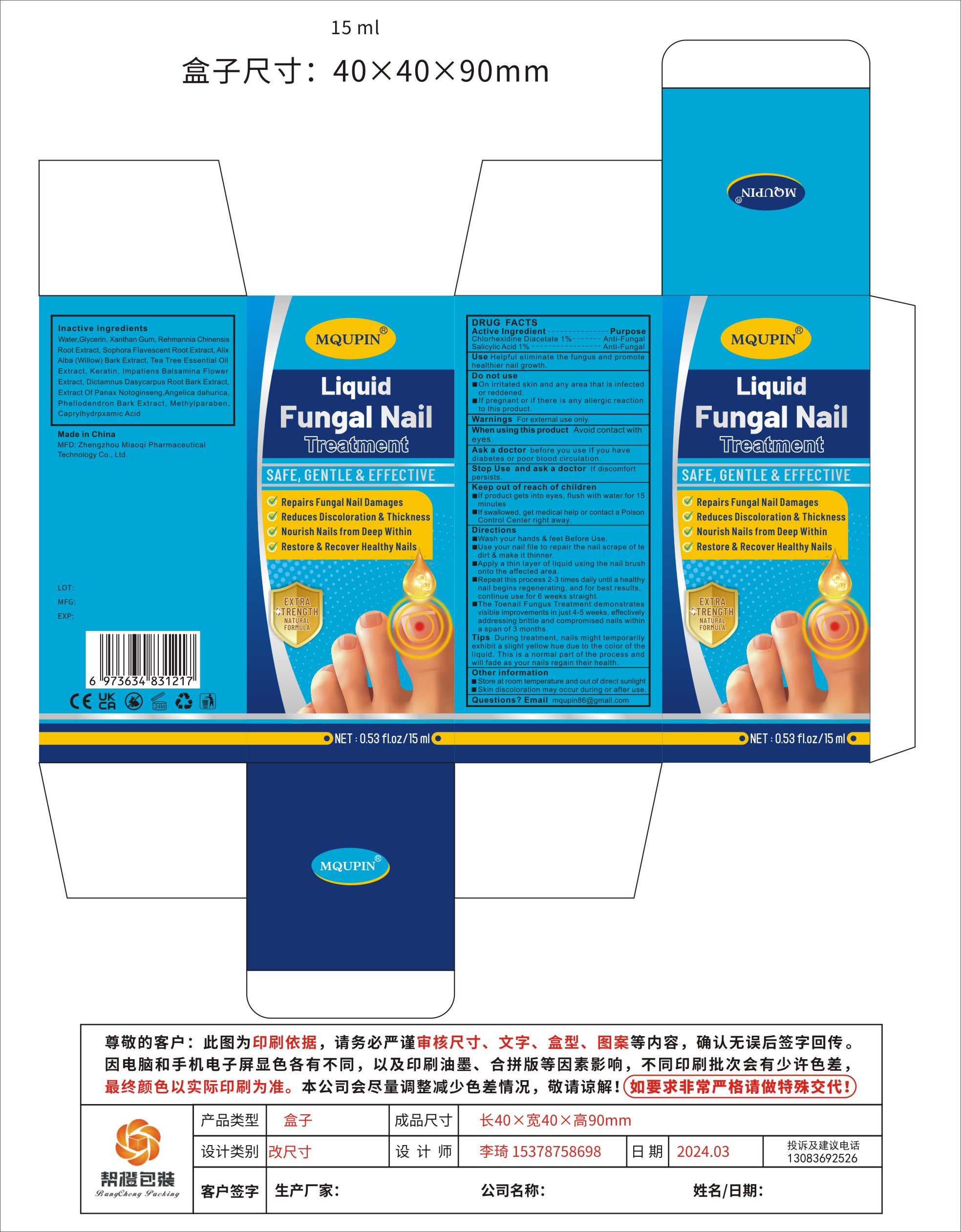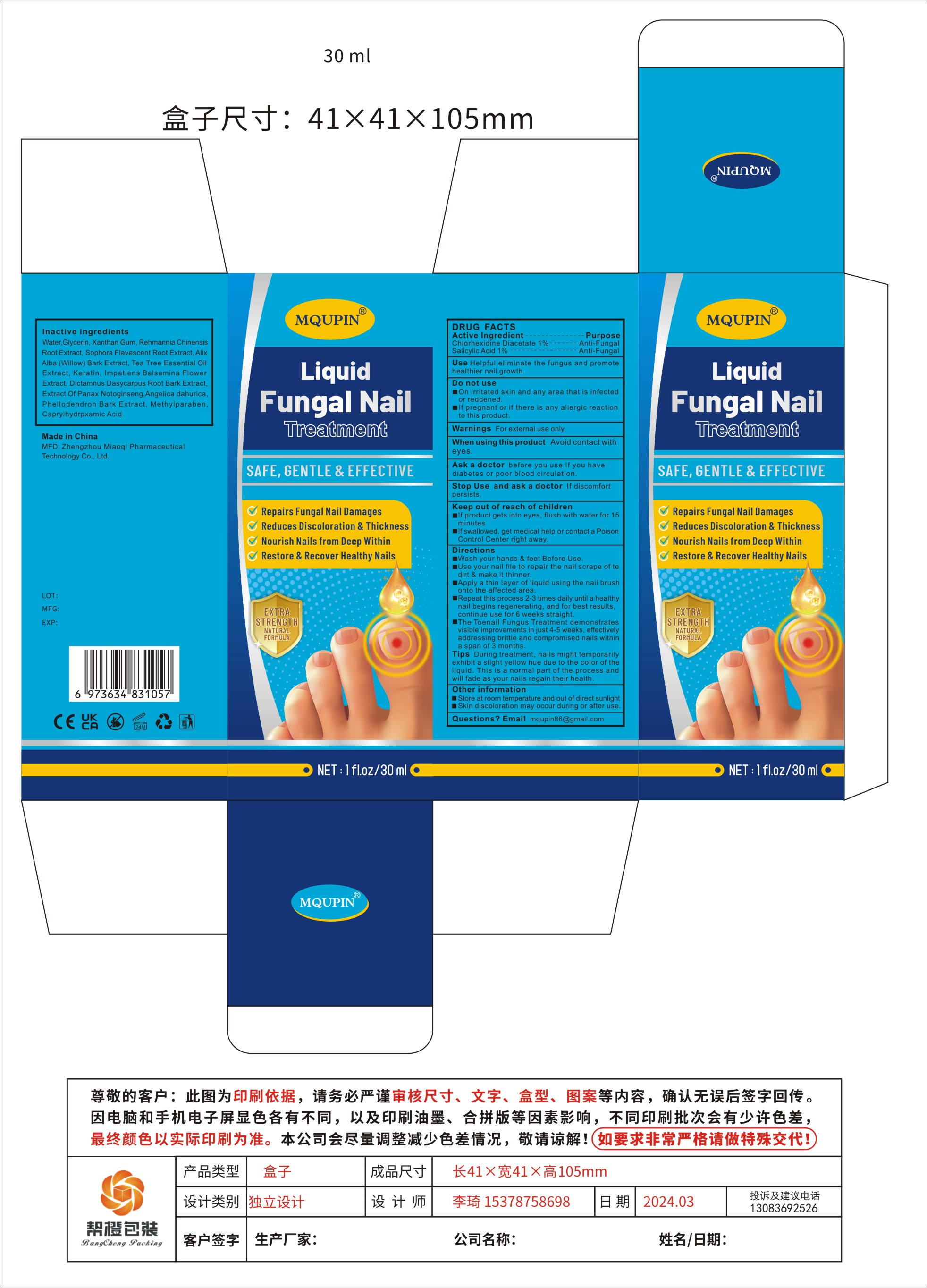 DRUG LABEL: MQUPIN Liquid Fungal Nail Treatment
NDC: 83781-009 | Form: LIQUID
Manufacturer: Zhengzhou Miaoqi Medical Technology Co., Ltd.
Category: otc | Type: HUMAN OTC DRUG LABEL
Date: 20240325

ACTIVE INGREDIENTS: SALICYLIC ACID 1 g/100 mL; CHLORHEXIDINE ACETATE 1 g/100 mL
INACTIVE INGREDIENTS: REHMANNIA GLUTINOSA ROOT; KERATIN, TYPE I CYTOSKELETAL 14; METHYLPARABEN; WATER; SALIX ALBA BARK; CAPRYLHYDROXAMIC ACID; GLYCERIN; PANAX NOTOGINSENG TOP; TEA TREE OIL; PHELLODENDRON AMURENSE BARK; XANTHAN GUM; ANGELICA DAHURICA SEED; IMPATIENS BALSAMINA FLOWER; DICTAMNUS DASYCARPUS ROOT BARK; SOPHORA FLAVESCENS ROOT

83781-009

Active Ingredient

Chlorhexidine Diacetate 1%
Salicylic Acid 1%

Purpose

Anti-Fungal

Use

Helpful eliminate the fungus and promote healthier nail growth.

Warnings

For external use only.

Do not use

■On irritated skin and any area that is infected or reddened.
■If pregnant or if there is any allergic reaction to this product.

When Using

Avoid contact with eyes.

Stop Use

If discomfort persists.

Ask Doctor

before you use If you have diabetes or poor blood circulation.
If discomfort persists.

Keep Out Of Reach Of Children

■If product gets into eyes, flush with water for 15 minutes
■If swallowed, get medical help or contact a Poison Control Center right away.

Directions

■Wash your hands & feet Before Use.
■Use your nail file to repair the nail scrape of te dirt & make it thinner.
■Apply a thin layer of liquid using the nail brush onto the affected area.
■Repeat this process 2-3 times daily until a healthy nail begins regenerating, and for best results, continue use for 6 weeks straight.
■The Toenail Fungus Treatment demonstrates visible improvements in just 4-5 weeks, effectively addressing brittle and compromised nails within a span of 3 months.

Other information

■Store at room temperature and out of direct sunlight
■Skin discoloration may occur during or after use.

Inactive ingredients

Water, Glycerin, Xanthan Gum, Rehmannia Chinensis Root Extract, Sophora Flavescent Root Extract, Alix Alba (Willow) Bark Extract, Tea Tree Essential Oil Extract, Keratin, Impatiens Balsamina Flower Extract, Dictamnus Dasycarpus Root Bark Extract, Extract Of Panax Notoginseng, Angelica dahurica, Phellodendron Bark Extract, Methylparaben, Caprylhydrpxamic Acid

Questions

mqupin86@gmail.com